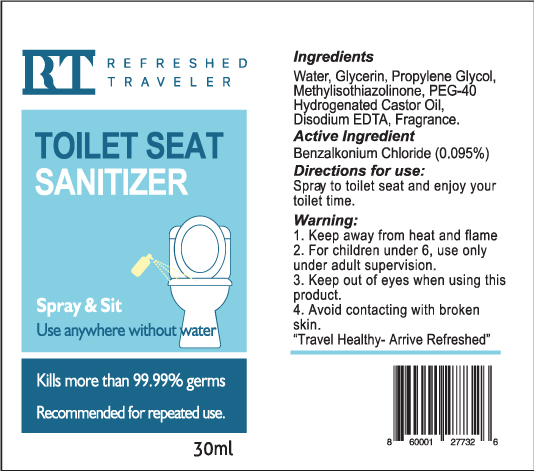 DRUG LABEL: Benzalkonium Chloride
NDC: 72920-2023 | Form: LIQUID
Manufacturer: Plane It Safe LLC
Category: otc | Type: HUMAN OTC DRUG LABEL
Date: 20211224

ACTIVE INGREDIENTS: BENZALKONIUM CHLORIDE 30 mg/30 mL
INACTIVE INGREDIENTS: WATER

Sanitizer Spray

Warning

Warning: 1. Keep away from heat and flame 2. For children under 6, use only under adult supervision. 3. Keep out of eyes when using this product. 4. Avoid contacting with broken skin.

Inactive

Water, Propylene Glycol, Glycerin, Methylisothiazolinone, Disodium EDTA.

Use

Spray & Sit

Active Ingredient:

Benzethonium Chloride (0.1%)

Directions:

Spray on toilet seat and sit

Uses:

Spray and sit

Keep out of reach of children

Purpose:

Kills bacteria on toilet seats

Toilet Seat Spray

Kills 99.99% of germs

Spray and sit

Use anywhere without water

Recommended for repeated use

Ingredients Water, Propylene Glycol, Glycerin, Methylisothiazolinone, Disodium EDTA. Active Ingredient Benzalkonium Chloride (0.095%) Directions for use: Spray to toilet seat and enjoy your toilet time. Warning: 1. Keep away from heat and flame 2. For children under 6, use only under adult supervision. 3. Keep out of eyes when using this product. 4. Avoid contacting with broken skin.